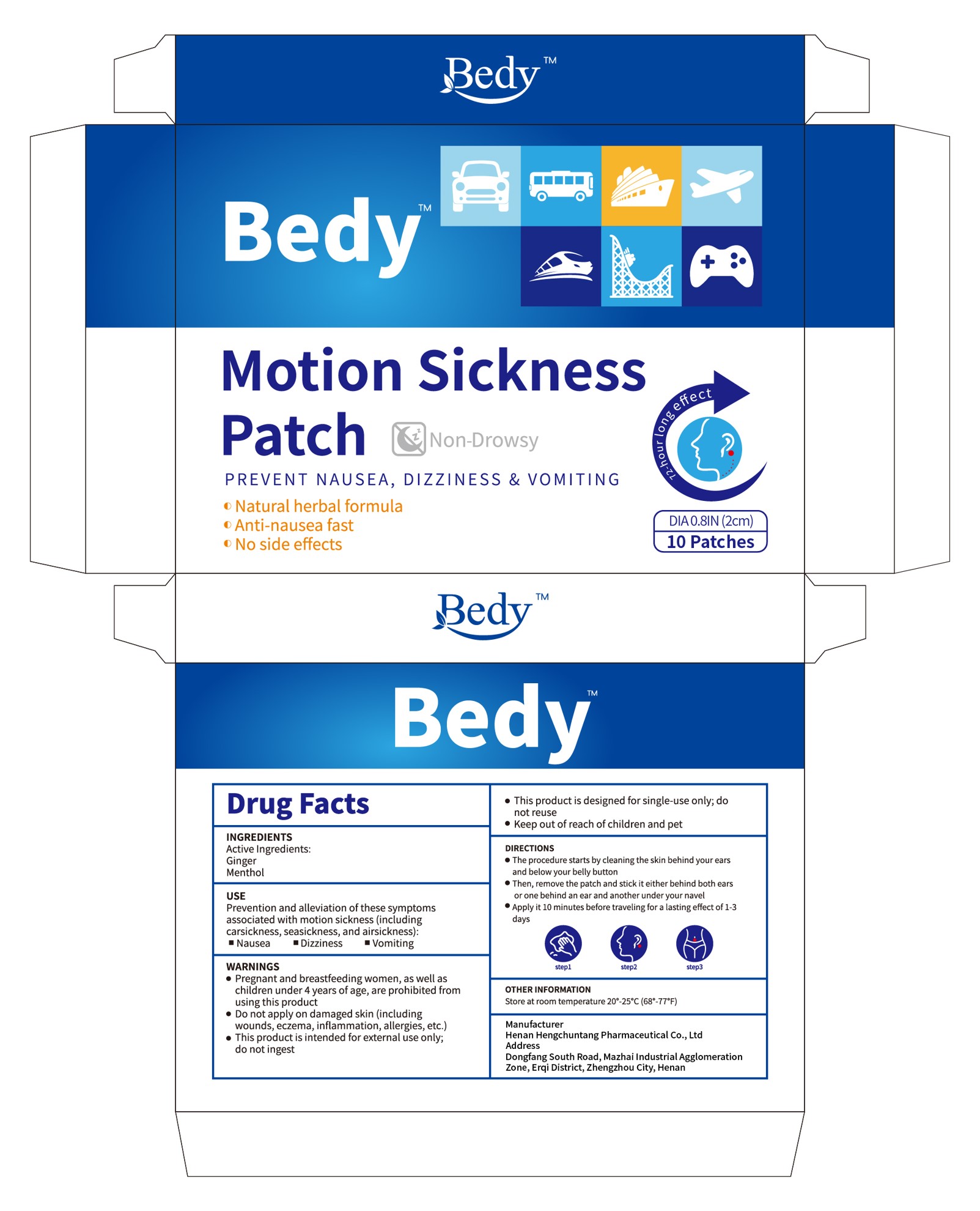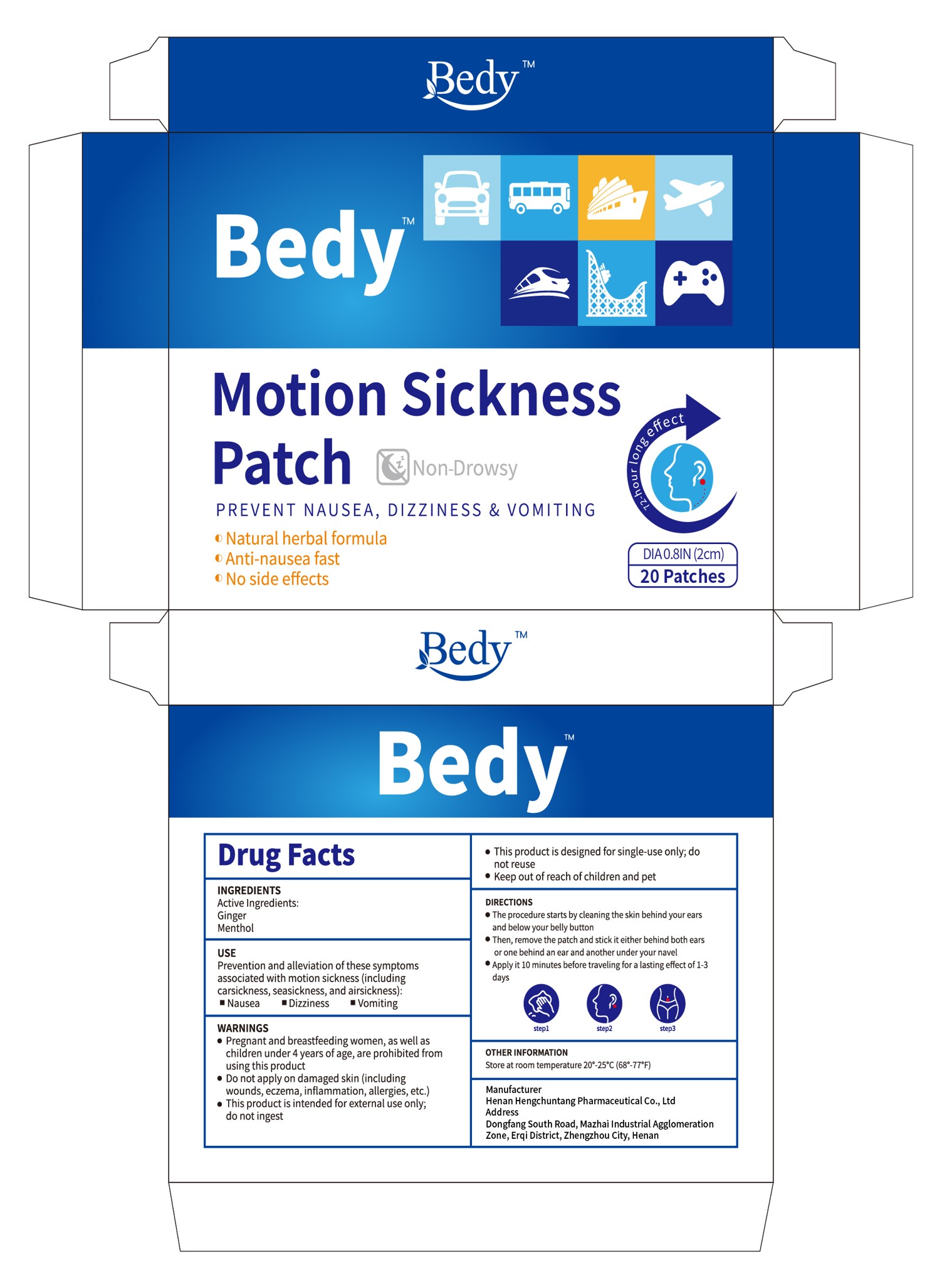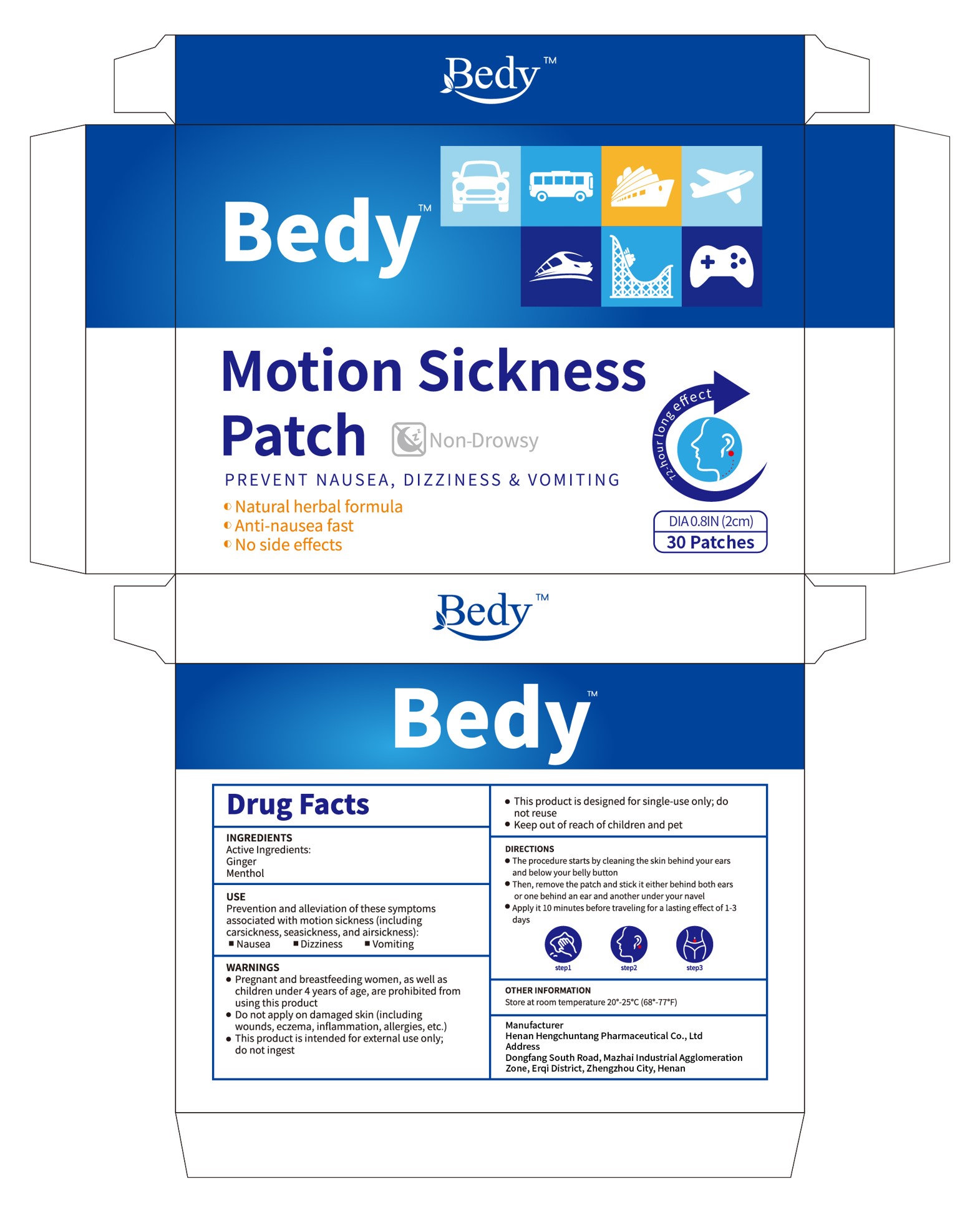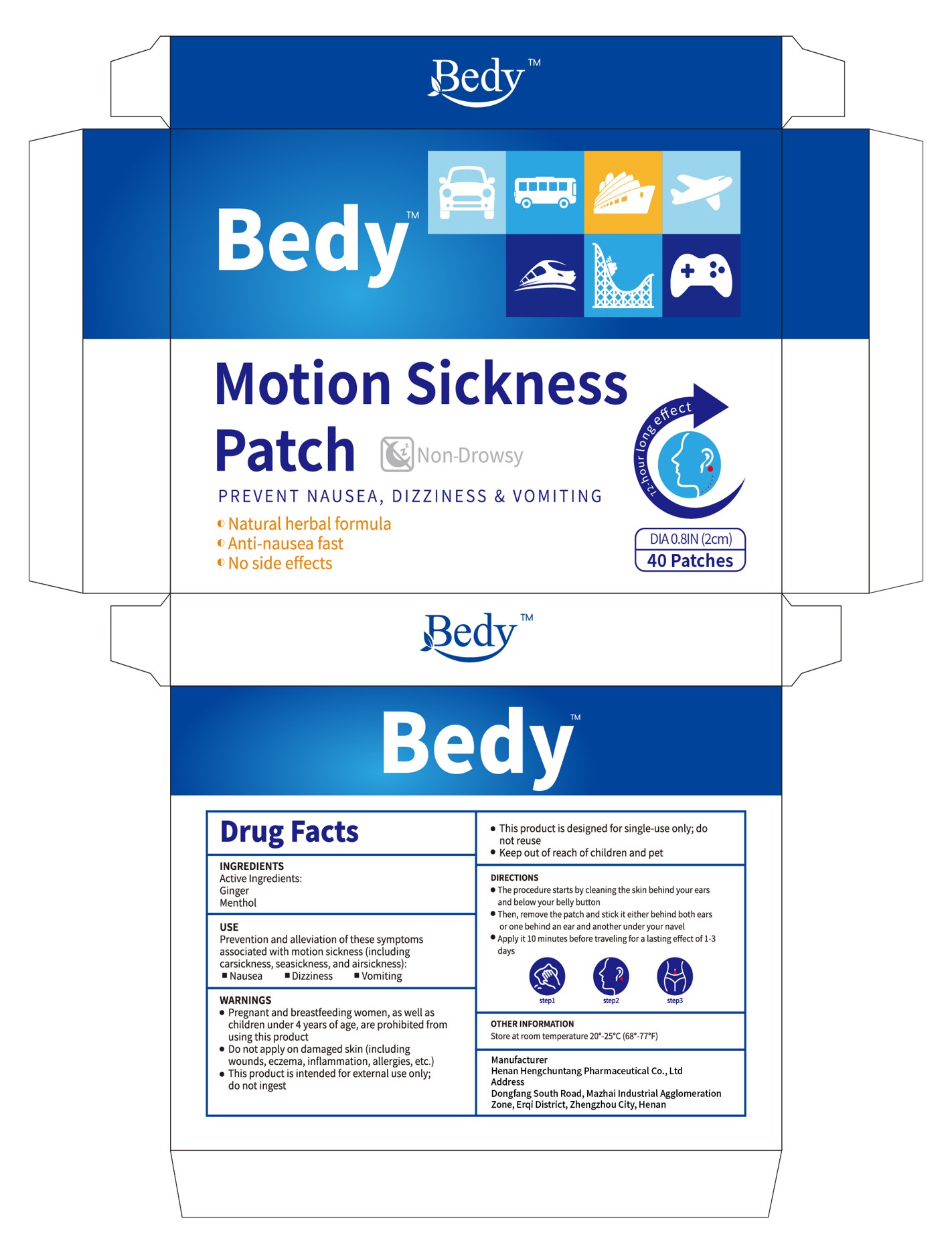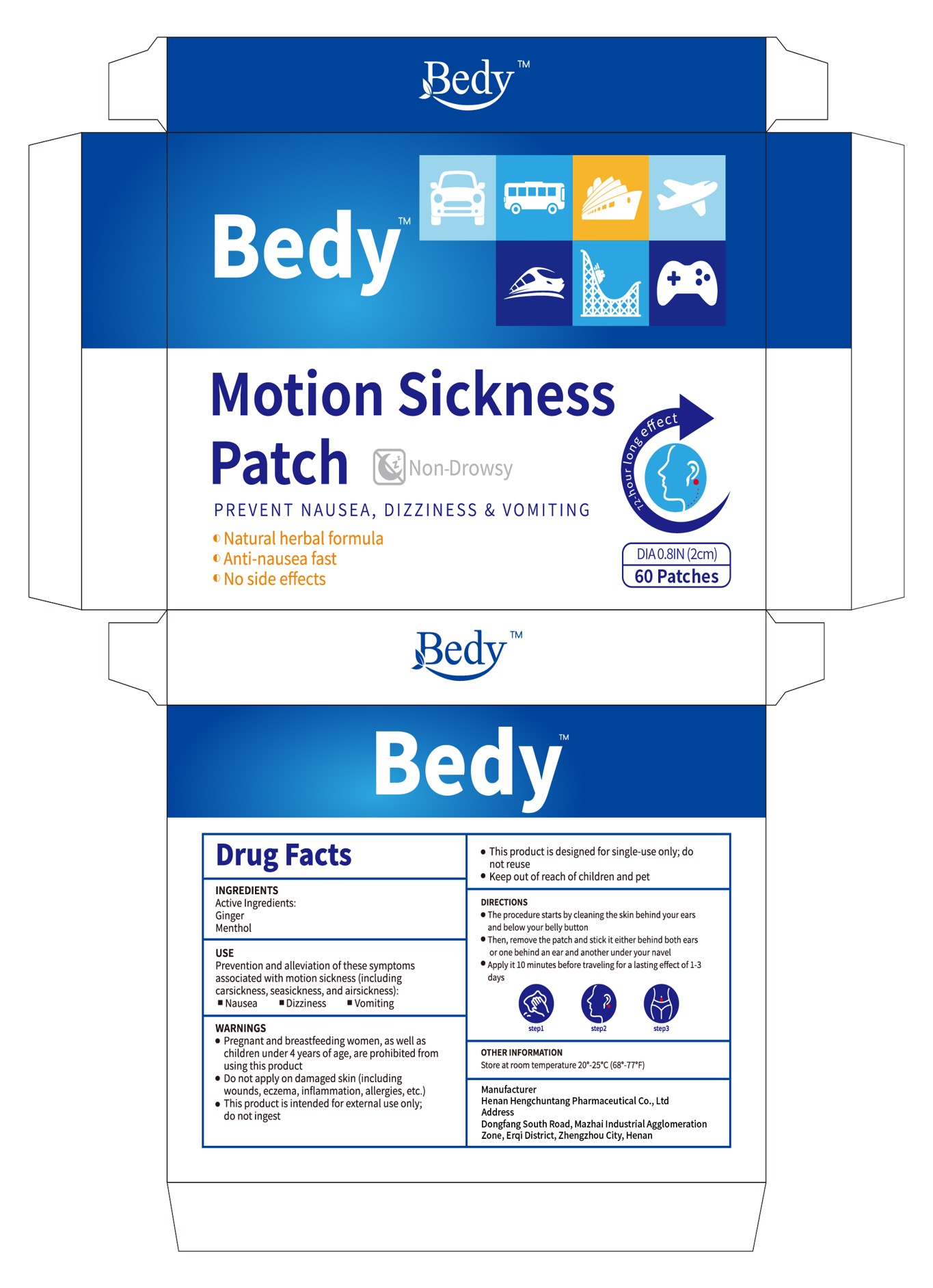 DRUG LABEL: Bedy motion sickness
NDC: 85152-002 | Form: PATCH
Manufacturer: Henan Hengchuntang Pharmaceutical Co., Ltd
Category: otc | Type: HUMAN OTC DRUG LABEL
Date: 20250215

ACTIVE INGREDIENTS: GINGER 1 g/100 g; MENTHOL 2 g/100 g
INACTIVE INGREDIENTS: ETHYLENE-VINYL ACETATE COPOLYMER (28% VINYL ACETATE); COTTON

INGREDIENTSActive

Ginger

Menthol

Inactive ingredients

EVA-28
COTTON

Purpose

PREVENT NAUSEA,DIZZINESS &VOMITING
o Natural herbal formula
o Anti-nausea fast
o No side effects

When using this product

Then, remove the patch and stick it either behind both earsor one behind an ear and another under your navel

Do not use

Pregnant women, breastfeeding mothers, children under the age of4 should not use.Do
not use if the skin has abnormalities, wounds, eczema, inflammation, allergies.Please
keep it out of reach of children and pets.

keep out of children

Please keep it out of reach of children and pets.
For external use only.

Dosage

Apply it 10 minutes before traveling for a lasting effect of 1-3days

warning

Pregnant women, breastfeeding mothers,
children under the age of 4 should not use
.Do not use if the skin has abnormalities, wounds, eczema, inflammation, allergies.
Please keep it out of reach of children and pets.
For external use only.

Directions

1.Tear open the package, take out the patch, peel off the white anti-adhesive layer, and
stick the patchbehind the ear or the navel (please dry the sweat from the ear and the
navel).
2.Use it 10 minutes before boarding a car, airplane or boat